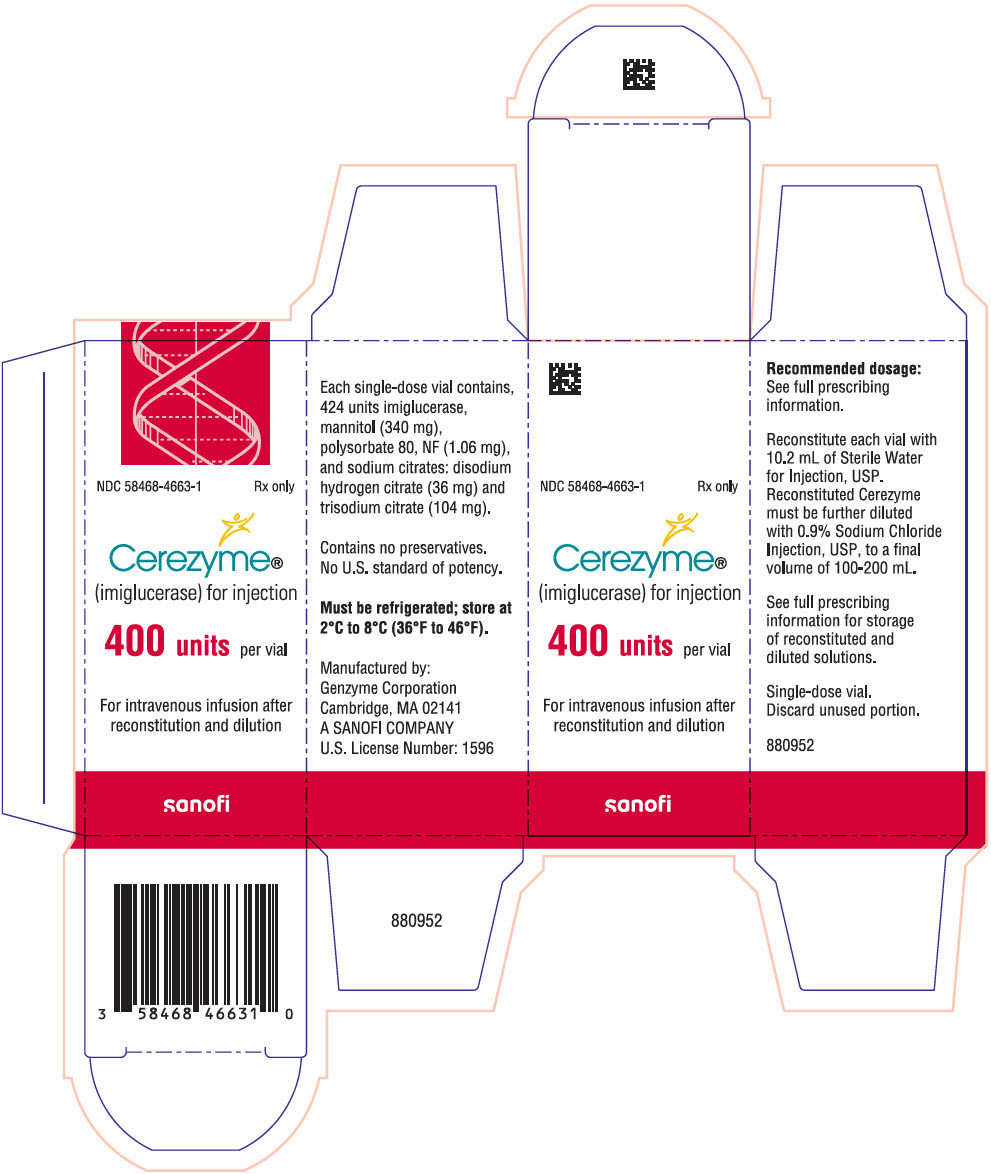 DRUG LABEL: Cerezyme
NDC: 58468-4663 | Form: INJECTION, POWDER, LYOPHILIZED, FOR SOLUTION
Manufacturer: Genzyme Corporation
Category: prescription | Type: HUMAN PRESCRIPTION DRUG LABEL
Date: 20251222

ACTIVE INGREDIENTS: IMIGLUCERASE 40 U/1 mL
INACTIVE INGREDIENTS: MANNITOL 32.08 mg/1 mL; TRISODIUM CITRATE DIHYDRATE 9.81 mg/1 mL; DISODIUM HYDROGEN CITRATE 3.4 mg/1 mL; POLYSORBATE 80 0.1 mg/1 mL

HIGHLIGHTS OF PRESCRIBING INFORMATION

These highlights do not include all the information needed to use CEREZYME® safely and effectively. See full prescribing information for CEREZYME.
CEREZYME (imiglucerase) for injection, for intravenous use
Initial U.S. Approval: 1994

WARNING: HYPERSENSITIVITY REACTIONS INCLUDING ANAPHYLAXIS

See full prescribing information for complete boxed warning.

- Anaphylaxis has occurred during the early course of enzyme replacement therapy and after extended duration of therapy. (5.1)
- Initiate CEREZYME in a healthcare setting with appropriate medical monitoring and support measures, including access to cardiopulmonary resuscitation equipment. (5.1)
- If a severe hypersensitivity reaction (e.g., anaphylaxis) occurs, discontinue CEREZYME and immediately initiate appropriate medical treatment, including use of epinephrine. (5.1)

RECENT MAJOR CHANGES

Indications and Usage (1) | 1/2026
Dosage and Administration (2.3, 2.4, 2.5) | 1/2026
Warnings and Precautions (5.1, 5.2) | 1/2026

1 INDICATIONS AND USAGE

CEREZYME is a hydrolytic lysosomal glucocerebrosidase-specific enzyme indicated for the treatment of non-central nervous system (CNS) manifestations of Type 1 or Type 3 Gaucher disease in adults and pediatric patients. (1)

2 DOSAGE AND ADMINISTRATION

- Administer CEREZYME under the supervision of a healthcare provider knowledgeable in the management of hypersensitivity reactions including anaphylaxis. (2.1)
- The recommended dosage is 2.5 units/kg three times a week to 60 units/kg once every two weeks administered intravenously. (2.2)
- Titrate the dosage based on disease severity and therapeutic goals for the patient. (2.2)
- See the full prescribing information for dosage modifications due to hypersensitivity reactions and/or IARs. (2.3)
- See the full prescribing information for preparation and administration instructions. (2.4, 2.5)

3 DOSAGE FORMS AND STRENGTHS

For injection: 400 units of imiglucerase as a lyophilized powder in a single-dose vial. (3)

4 CONTRAINDICATIONS

None. (4)

5 WARNINGS AND PRECAUTIONS

Infusion-Associated Reactions (IARs): If a severe IAR occurs, discontinue CEREZYME immediately and initiate appropriate medical treatment. (5.2)

6 ADVERSE REACTIONS

- Adverse reactions reported in adults and pediatric patients include back pain, chills, dizziness, fatigue, headache, hypersensitivity reactions, nausea, pyrexia, and vomiting. (6.1)

To report SUSPECTED ADVERSE REACTIONS, contact Genzyme at 1-800-633-1610 or FDA at 1-800-FDA-1088 or www.fda.gov/medwatch.

FULL PRESCRIBING INFORMATION

WARNING: HYPERSENSITIVITY REACTIONS INCLUDING ANAPHYLAXIS

Patients treated with enzyme replacement therapies have experienced life-threatening hypersensitivity reactions, including anaphylaxis. Anaphylaxis has occurred during the early course of enzyme replacement therapy and after extended duration of therapy.

Initiate CEREZYME in a healthcare setting with appropriate medical monitoring and support measures, including access to cardiopulmonary resuscitation equipment. If a severe hypersensitivity reaction (e.g., anaphylaxis) occurs, discontinue CEREZYME and immediately initiate appropriate medical treatment, including use of epinephrine. Inform patients of the symptoms of life-threatening hypersensitivity reactions, including anaphylaxis and to seek immediate medical care should symptoms occur [see Warnings and Precautions (5.1)].

1 INDICATIONS AND USAGE

CEREZYME is indicated for the treatment of non-central nervous system (CNS) manifestations of Type 1 or Type 3 Gaucher disease in adults and pediatric patients.

2 DOSAGE AND ADMINISTRATION

2.1 Recommendations Prior to CEREZYME Treatment

Administer CEREZYME under the supervision of a healthcare provider knowledgeable in the management of hypersensitivity reactions including anaphylaxis [see Warnings and Precautions (5.1)].

Initiate CEREZYME in a healthcare setting with appropriate medical monitoring and support measures, including access to cardiopulmonary resuscitation equipment [see Warnings and Precautions (5.1)].

For patients who experience hypersensitivity reactions to CEREZYME, premedicate with antihistamines and/or corticosteroids. Monitor patients for the occurrence of new hypersensitivity reactions [see Warnings and Precautions (5.1)].

2.2 Recommended Dosage and Administration

Ensure physicians knowledgeable in the management of patients with Gaucher disease direct therapy with CEREZYME.

The recommended dosage of CEREZYME is 2.5 units/kg three times a week to 60 units/kg once every two weeks administered intravenously.

Titrate the dosage based on disease severity and therapeutic goals for the patient.

For adults and pediatric patients weighing greater than 20 kg, infuse the diluted CEREZYME solution over 1 to 2 hours [see Dosage and Administration (2.5)].

For pediatric patients weighing 20 kg or less, infuse the diluted CEREZYME solution over 2 hours [see Dosage and Administration (2.5)].

2.3 Dosage and Administration Modifications Due to Hypersensitivity Reactions and/or Infusion-Associated Reactions

If a severe hypersensitivity reaction (e.g., anaphylaxis) or a severe infusion-associated reaction (IAR) occurs, discontinue CEREZYME and immediately initiate appropriate medical treatment [see Warnings and Precautions (5.1, 5.2)].

If a mild or moderate hypersensitivity reaction or a mild or moderate IAR occurs, consider decreasing the infusion rate, temporarily stopping the infusion, and/or administering antihistamines, antipyretics, and/or corticosteroids [see Warnings and Precautions (5.1, 5.2)].

2.4 Preparation Instructions

Use aseptic technique during preparation.

Reconstitution

1. Determine the number of CEREZYME vials to be reconstituted based on the individual patient's dosage regimen and remove vial(s) from the refrigerator [see Dosage and Administration (2.1)].
2. Reconstitute each vial of CEREZYME by slowly injecting 10.2 mL of Sterile Water for Injection, down the inside wall of each vial.
3. Roll and tilt the vial to allow the powder to dissolve completely. Visually inspect the reconstituted solution for particulate matter and discoloration. Discard if opaque particles or discoloration are observed. After reconstitution, each vial will yield CEREZYME at a concentration of 40 units/mL.
4. Withdraw the required volume of CEREZYME from the vial(s).

Dilution

1. Dilute the CEREZYME solution for infusion promptly with 0.9% Sodium Chloride Injection to a final volume that is calculated based on prescribed dose.
2. For CEREZYME administered at a dose of 60 units/kg, use the following final volumes (see Table 1).
  - For patients weighing between 1.5 kg and less than 6 kg, dilute CEREZYME to a final volume of 12 mL in a syringe for infusion.
  - For patients weighing between 6 kg and less than 13 kg, dilute CEREZYME to a final volume of 26 mL in a syringe for infusion.
  - For patients weighing between 13 kg and less than or equal to 20 kg, dilute CEREZYME to a final volume of 100 mL in an infusion bag.
  - For patients weighing greater than 20 kg and less than or equal to 100 kg, dilute CEREZYME to a final volume of 200 mL in an infusion bag.
  - For patients weighing greater than 100 kg, dilute CEREZYME to a final volume of 400 mL in an infusion bag.
3. If CEREZYME is prescribed at a dose lower than 60 units/kg, dilute the required total units of reconstituted CEREZYME (at a concentration of 40 units/mL) with 0.9% Sodium Chloride Injection to a final concentration between 6 units/mL and 30 units/mL inclusive. If the determined dose of CEREZYME translates into a total volume of 26 mL or less, administer using a syringe for infusion via a syringe pump.
4. For accuracy of dilution, if less than 2 mL of reconstituted CEREZYME (40 units/mL) is needed for the preparation of the determined dose, prepare a larger final volume of CEREZYME for infusion initially maintaining the final concentration of the diluted CEREZYME solution between 6 units/mL to 30 units/mL. Subsequently, discard the excess volume and administer only the volume of CEREZYME solution corresponding to the prescribed dose.
5. Gently invert the syringe for infusion or the infusion bag to mix the solution. Throughout CEREZYME preparation, avoid vigorous shaking, agitation and foaming.

Vials are for single dose only. Discard any unused solution.

2.5 Administration Instructions

Visually inspect the diluted solution prior to administration of the final product for particulate matter and discoloration. Slight flocculation of protein particles (described as thin translucent fibers) may occur after dilution and does not affect the quality of the product.

Administer CEREZYME as an intravenous infusion with a 0.2 micron in-line low protein-binding filter.

Table 1: Total Infusion Volumes and Infusion Time for CEREZYME
Patient Weight | Total Infusion Volume [Final concentration of diluted CEREZYME solution is between 6 units/mL and 30 units/mL.] | Infusion Time | Maximum Infusion Rate
1.5 kg to < 6 kg | 12 mL | 2 hours | 6 mL/hour
6 kg to < 13 kg | 26 mL | 2 hours | 13 mL/hour
13 kg to ≤ 20 kg | 100 mL | 2 hours | 50 mL/hour
> 20 kg to ≤ 100 kg | 200 mL | 1 to 2 hours | 200 mL/hour
> 100 kg | 400 mL | 1 to 2 hours | 400 mL/hour

2.6 Storage and Handling

- If the reconstituted CEREZYME vial is not used immediately:
  - Refrigerate the reconstituted solution at 2°C to 8°C (36°F to 46°F) or store at room temperature at 20°C to 25°C (68°F to 77°F) for up to 12 hours.
- Refrigerate the diluted solution at 2°C to 8°C (36°F to 46°F) for up to 24 hours.

3 DOSAGE FORMS AND STRENGTHS

For injection: 400 units of imiglucerase as a white to off-white lyophilized powder in a single-dose vial for reconstitution.

4 CONTRAINDICATIONS

None.

5 WARNINGS AND PRECAUTIONS

5.1 Hypersensitivity Reactions Including Anaphylaxis

Life-threatening hypersensitivity reactions, including anaphylaxis, have been reported in patients treated with enzyme replacement therapies, including CEREZYME. In addition, other hypersensitivity reactions have included pruritus, flushing, urticaria, angioedema, chest discomfort, dyspnea, cough, cyanosis, tachycardia, and hypotension [see Adverse Reactions (6.1)]. Patients with antibody to imiglucerase have a higher risk of hypersensitivity reactions. Conversely, not all patients with symptoms of hypersensitivity have detectable IgG antibody. Consider periodic monitoring of patients during the first year of treatment for IgG antibody formation [see Adverse Reactions (6.2)].

Anaphylaxis has occurred during the early course of enzyme replacement therapy and after extended duration of therapy. Administer CEREZYME under the supervision of a healthcare provider knowledgeable in the management of hypersensitivity reactions including anaphylaxis. Initiate CEREZYME in a healthcare setting with appropriate medical monitoring and support measures, including access to cardiopulmonary resuscitation equipment.

If a severe hypersensitivity reaction (e.g., anaphylaxis) occurs, discontinue CEREZYME and immediately initiate appropriate medical treatment, including use of epinephrine. Consider the risks and benefits of re-administering CEREZYME following severe hypersensitivity reactions (including anaphylaxis). If the decision is made to re-administer CEREZYME, consider decreasing the infusion rate and administering antihistamines, antipyretics, and/or corticosteroids. Monitor patients for the occurrence of new signs and symptoms of a severe hypersensitivity reaction.

If a mild or moderate hypersensitivity reaction occurs, consider decreasing the infusion rate, temporarily stopping the infusion, and/or administering antihistamines, antipyretics, and/or corticosteroids.

Inform patients of the symptoms of life-threatening hypersensitivity reactions, including anaphylaxis and to seek immediate medical care should symptoms occur.

5.2 Infusion-Associated Reactions

Infusion-associated reactions (IARs) such as angioedema, pruritus, rash, urticaria, chest discomfort, chills, fatigue, infusion-site burning, infusion-site discomfort, infusion-site swelling, pyrexia and hypertension have been observed in patients treated with CEREZYME [see Adverse Reactions (6.1)].

If a severe IAR occurs, discontinue CEREZYME and immediately initiate appropriate medical treatment. Consider the risks and benefits of re-administering CEREZYME following a severe IAR.

If a mild or moderate IAR occurs, consider decreasing the infusion rate, temporarily stopping the infusion, and/or administering antihistamines, antipyretics, and/or corticosteroids.

6 ADVERSE REACTIONS

The following clinically significant adverse reactions are described elsewhere in the labeling:

- Hypersensitivity Reactions Including Anaphylaxis [see Warnings and Precautions (5.1)]
- Infusion-Associated Reactions [see Warnings and Precautions (5.2)]

6.1 Clinical Trials and Postmarketing Experience

The following adverse reactions associated with the use of imiglucerase were identified in clinical studies or postmarketing reports. Because some of these reactions were reported voluntarily from a population of uncertain size, it is not always possible to reliably estimate their frequency or establish a causal relationship to drug exposure.

See Table 2 for adverse reactions occurring in adults and pediatric patients treated with CEREZYME in clinical trials and the postmarketing setting.

Table 2: Adverse Reactions in Adults and Pediatric Patients Treated with CEREZYME
 | Adverse Reactions
Nervous system disorders | dizziness, headache
Cardiac disorders | tachycardia
Vascular disorders | cyanosis, [Signs and symptoms suggestive of hypersensitivity reactions including anaphylaxis [see Warnings and Precautions (5.1)] and other infusion-associated reactions [see Warnings and Precautions (5.2)].] flushing, hypotension, hypertension
Respiratory, thoracic and mediastinal disorders | cough, dyspnea, pneumonia, pulmonary hypertension
Gastrointestinal disorders | abdominal pain, diarrhea, nausea, vomiting
Immune system disorders | anaphylaxis, hypersensitivity
Skin and subcutaneous tissue disorders | angioedema, pruritus, rash, urticaria
Musculoskeletal and connective tissue disorders | back pain
General disorders and administration site conditions | chest discomfort, chills, fatigue, infusion-site burning, infusion-site discomfort, infusion-site swelling, pyrexia

6.2 Immunogenicity

The observed incidence of anti-drug antibodies (ADA) is highly dependent on the sensitivity and specificity of the assay. Differences in assay methods preclude meaningful comparisons of the incidence of ADA in the studies described below with the incidence of ADA in other studies, including those of CEREZYME or of other imiglucerase products.

Approximately 15% of patients treated and tested to date have developed IgG antibody to CEREZYME during the first year of therapy. Patients who developed IgG antibody did so largely within 6 months of treatment and rarely developed antibodies to CEREZYME after 12 months of therapy. Approximately 46% of patients with detectable IgG antibodies experienced symptoms of hypersensitivity. Patients with antibody to CEREZYME have higher risk of hypersensitivity reaction [see Warnings and Precautions (5.1)]. Patients who developed IgG antibody to CEREZYME had increased elimination half-life compared to patients without antibody [see Clinical Pharmacology (12.3)].

8 USE IN SPECIFIC POPULATIONS

8.1 Pregnancy

Pregnancy Exposure Registry

There is a pregnancy exposure registry that monitors pregnancy outcomes in women exposed to CEREZYME during pregnancy. Pregnant women exposed to CEREZYME and health care providers are encouraged to contact the Gaucher patient registry at 1-800-745-4447, extension 15500 or visit www.registrynxt.com.

Risk Summary

Available data on more than 500 pregnancies from the international Gaucher Disease registry, postmarketing reports, published observational studies and case reports with CEREZYME or non–US-licensed imiglucerase use in pregnant women have not identified a drug-associated risk of major birth defects, miscarriage, or other adverse maternal or fetal outcomes. There are risks associated with symptomatic Type I Gaucher disease in pregnancy (see Clinical Considerations). No animal reproduction studies have been conducted with imiglucerase.

The estimated background risk of major birth defects and miscarriage in the indicated population is unknown. All pregnancies have a background risk of birth defect, loss, or other adverse outcomes. In the U.S. general population, the estimated background risk of major birth defects and miscarriage in clinically recognized pregnancies is 2% to 4% and 15% to 20%, respectively.

Clinical Considerations

Disease-Associated Maternal and/or Embryo/Fetal Risk

Pregnancy may exacerbate existing Type 1 Gaucher disease symptoms or result in new disease manifestations. Untreated symptomatic Type 1 Gaucher disease may lead to complications during pregnancy, including hepatosplenomegaly, which can interfere with the normal growth of a pregnancy and thrombocytopenia, which can lead to excessive bleeding.

8.2 Lactation

Risk Summary

Available published literature suggests a small amount of imiglucerase is present in breast milk immediately following an infusion of imiglucerase. Published case reports and postmarketing reports of breastfed infants have not reported adverse effects due to CEREZYME exposure. There are no data available on the effects on milk production. The developmental and health benefits of breastfeeding should be considered along with the mother's clinical need for CEREZYME and any potential adverse effects on the breastfed infant from imiglucerase or from the underlying maternal condition.

Lactating women with Gaucher disease treated with CEREZYME should be encouraged to enroll in the Gaucher patient registry [see Use in Specific Populations (8.1)].

8.4 Pediatric Use

The safety and effectiveness of CEREZYME for the treatment of non-CNS manifestations of Type 1 or Type 3 Gaucher disease have been established in pediatric patients. Use of CEREZYME for the treatment of non-CNS manifestations of Type 1 Gaucher disease is supported by evidence from adequate and well-controlled trials in adults and pediatric patients 12 years of age and older and additional safety and efficacy data from an observational study of Type 1 Gaucher disease in pediatric patients [see Adverse Reactions (6.1) and Clinical Studies (14)].

Use of CEREZYME for the treatment of non-CNS manifestations of Type 3 Gaucher disease is supported by evidence from adequate and well-controlled trials in adults and pediatric patients 12 years of age and older with Type I Gaucher disease and additional safety and efficacy data from an observational study of Type 3 Gaucher disease in adults and pediatric patients [see Adverse Reactions (6.1) and Clinical Studies (14)].

8.5 Geriatric Use

Among the patients with Type 1 Gaucher disease in Study 3 [see Clinical Studies (14)] who had hemoglobin or platelet count measurements 1 to 3 years after initiating CEREZYME (n = 1,053), 6% of patients were 65 and over and 1% were 75 and over. No overall differences in effectiveness of CEREZYME were observed between patients 65 years of age and older and younger adult patients with Type 1 Gaucher disease.

The safety evaluation for patients 65 years of age and older with Type 1 Gaucher disease was conducted using data from a pharmacovigilance database that collected individual case safety reports and did not reveal new safety findings. Clinical studies of CEREZYME did not include sufficient numbers of patients 65 years of age and older to detect differences in safety between older and younger adult patients with Type 1 Gaucher disease.

Clinical studies of CEREZYME did not include sufficient numbers of patients 65 years of age and older to detect differences in efficacy and safety between older and younger adult patients with Type 3 Gaucher disease.

11 DESCRIPTION

Imiglucerase is a hydrolytic lysosomal glucocerebrosidase-specific enzyme. It is an analogue of the human enzyme b-glucocerebrosidase (b-D-glucosyl-N-acylsphingosine glucohydrolase, E.C. 3.2.1.45), produced by recombinant DNA technology using mammalian cell culture (Chinese hamster ovary). Purified imiglucerase is a monomeric glycoprotein of 497 amino acids, containing 4 N-linked glycosylation sites (Mr=60,430). Imiglucerase differs from placental glucocerebrosidase by one amino acid at position 495, where histidine is substituted for arginine. The oligosaccharide chains at the glycosylation sites have been modified to terminate in mannose sugars. The modified carbohydrate structures on imiglucerase are somewhat different from those on placental glucocerebrosidase.

CEREZYME (imiglucerase) for injection is intended for intravenous use. It is supplied as a sterile, nonpyrogenic, white to off-white lyophilized powder for reconstitution with Sterile Water for Injection, USP. Each single-dose vial contains 424 units imiglucerase, mannitol (340 mg), polysorbate 80, NF (1.06 mg), and sodium citrates: disodium hydrogen citrate (36 mg) and trisodium citrate (104 mg).

An enzyme unit (U) is defined as the amount of enzyme that catalyzes the hydrolysis of 1 micromole of the synthetic substrate para-nitrophenyl-b-D-glucopyranoside (pNP-Glc) per minute at 37°C. Reconstituted solutions have a pH of approximately 6.1.

12 CLINICAL PHARMACOLOGY

12.1 Mechanism of Action

Gaucher disease is characterized by a deficiency of β-glucocerebrosidase activity, which results in accumulation of glucocerebroside in various tissues including liver, spleen, and bone marrow. The mannose sugars on imiglucerase mediate binding to and internalization by cells including macrophages. CEREZYME catalyzes the hydrolysis of glucocerebroside to glucose and ceramide.

12.2 Pharmacodynamics

No formal pharmacodynamic studies have been conducted with CEREZYME.

12.3 Pharmacokinetics

During one-hour intravenous infusions of four doses (7.5, 15, 30, 60 units/kg) of CEREZYME, steady-state enzymatic activity was achieved by 30 minutes. Following infusion, the half-life of plasma enzymatic activity ranged from 3.6 to 10.4 minutes. Plasma clearance ranged from 9.8 to 20.3 mL/min/kg (mean ± SD, 14.5 ± 4.0 mL/min/kg). The volume of distribution corrected for weight ranged from 0.09 to 0.15 L/kg (mean ± SD, 0.12 ± 0.02 L/kg). These variables do not appear to be influenced by dose or duration of infusion. However, only one or two patients were studied at each dose level and infusion rate.

Antidrug Antibody Effects on Pharmacokinetics

In patients who developed IgG antibody to CEREZYME, an apparent effect on serum enzyme levels resulted in diminished volume of distribution and clearance and increased elimination half-life compared to patients without antibody [see Adverse Reactions (6.2)].

13 NONCLINICAL TOXICOLOGY

13.1 Carcinogenesis, Mutagenesis, Impairment of Fertility

Carcinogenesis

Long-term studies in animals to evaluate carcinogenic potential have not been performed with imiglucerase.

Mutagenesis

Imiglucerase was negative in the Ames test.

Impairment of Fertility

An animal fertility study was not performed. No histopathological findings on reproductive organs were observed in 13-week toxicity studies conducted in rats and monkeys.

14 CLINICAL STUDIES

Study 1 was a randomized, double-blind, active-controlled clinical trial that enrolled 30 patients (17 male and 13 female) with Type 1 Gaucher disease. Patient ages ranged from 12 to 69 years, with a mean age of 38 years in the CEREZYME treatment group and a mean age of 28 years in the alglucerase treatment group at baseline. The inclusion criteria required patients to have a hemoglobin level of at least 1 g/dL below the lower limit of the normal range for their respective age and sex. Patients were randomized 1:1 to receive either CEREZYME 60 units/kg administered intravenously every other week or alglucerase for 6 months.

In Study 1, the primary efficacy parameters were an increase in hemoglobin concentration (at least 1 g/dL) and platelet count and a decrease in spleen and liver volume at 6 months. Efficacy results are shown in Table 3.

In Study 1, bone x-rays showed improvements in cortical thickness and lucencies in 7 of 11 CEREZYME-treated patients.

Table 3: Change from Baseline to Month 6 in Clinical Efficacy Parameters in a Randomized, Double-Blind Active-Controlled Trial of CEREZYME Compared to Alglucerase in Patients 12 Years of Age and Older with Gaucher Disease Type 1 (Study 1)
Clinical Parameter |  | CEREZYME (N=15) | Alglucerase (N=15) | Difference (CEREZYME – Alglucerase) [95% CI] [Confidence intervals were calculated using the t distribution (appropriate for small sample sizes) and the standard error of the difference in sample means (i.e., the pooled estimate of the common standard deviation, computed as the weighted average of the standard deviations in the two treatment groups); there was no evidence that the assumption of equal variances between the groups was violated.]
Hemoglobin concentration (g/dL) | Baseline | 10.7 | 10.9 | –
Hemoglobin concentration (g/dL) | Absolute Change from Baseline | 1.9 | 1.6 | 0.3 [-0.6, 1.3]
Platelet count (× 10^3/mm^3) | Baseline | 68.5 | 74.2 | –
Platelet count (× 10^3/mm^3) | Absolute Change from Baseline | 22.7 | 15.8 | 6.9 [-10.4, 24.1]
Liver volume (mL) | Baseline | 2521 | 2788 | –
Liver volume (mL) | Absolute Change from Baseline | -310 | -307 | -3 [-246, 240]
Liver volume (mL) | Percent Change from Baseline (%) | -11 | -10 | -1 [-9, 7]
Spleen volume (mL) | Baseline | 2369 | 2603 | –
Spleen volume (mL) | Absolute Change from Baseline | -902 | -874 | -28 [-652, 596]
Spleen volume (mL) | Percent Change from Baseline (%) | -35 | -30 | -5 [-14, 4]

In Study 2, an open-label extension study of Study 1, 29 patients with Type 1 Gaucher disease continued their assigned treatment for an additional 18 months. Patients were unblinded 3 months into Study 2 and those on alglucerase were allowed to cross-over to CEREZYME treatment. After total treatment duration of CEREZYME for 18–24 months, mean increase from baseline of Study 1 in hemoglobin was 2.4 g/dL, mean increase in platelet count was 40 ×10^3/mm^3, mean change in liver volume was -20%, and mean change in spleen volume was -57%.

The efficacy of CEREZYME for the treatment of non-CNS manifestations of Type 1 and Type 3 Gaucher disease was assessed in Study 3, an observational study, using data from the International Collaborative Gaucher Group (ICGG) Gaucher Disease Registry (NCT00358943). Study 3 included patients with Type 1 or Type 3 Gaucher disease who were treated with CEREZYME as initial therapy with an index clinical assessment and one or more follow-up clinical assessments. Study 3 was a baseline-controlled analysis in patients with Type 1 Gaucher disease (19 weeks to 87 years of age) and patients with Type 3 Gaucher disease (7 weeks to 54 years of age) who received CEREZYME intravenously as prescribed by their physicians (initiated treatment between 1992–2021). After approximately two years (1 to 3 years) of CEREZYME treatment in patients with Type 1 and 3 Gaucher disease, mean changes from baseline in the following measures showed improvement: hemoglobin, platelet count, liver volume, spleen volume, and height Z-score.

- Among 1,052 Type 1 Gaucher disease patients, mean baseline hemoglobin was 11.8 g/dL and mean increase from baseline was 1.5 g/dL (95% CI: 1.4, 1.5).
- Among 1,053 Type 1 Gaucher disease patients, mean baseline platelet count was 128×10^3/mm^3 and mean increase from baseline was 64×10^3/mm^3 (95% CI: 59.6, 67.9).
- Among 118 Type 3 Gaucher disease patients, mean baseline hemoglobin levels were 10 g/dL and mean increase from baseline was 1.8 g/dL (95% CI: 1.5, 2.1).
- Among 116 Type 3 Gaucher disease patients, mean baseline platelet count was 149×10^3/mm^3 and mean increase from baseline was 105×10^3/mm^3 (95% CI: 87.4, 122.4).

The 2-year summaries include measurements within 1 to 3 years after treatment initiation due to the lack of predefined data collection timepoints in the registry.

16 HOW SUPPLIED/STORAGE AND HANDLING

CEREZYME (imiglucerase) for injection is supplied as a white to off-white lyophilized powder in a carton containing one single-dose vial: NDC 58468-4663-1. Each vial contains 400 units of imiglucerase. CEREZYME does not contain any preservatives.

STORAGE AND HANDLING

Store refrigerated at 2°C to 8°C (36°F to 46°F).

For storage of reconstituted and diluted solution [see Dosage and Administration (2.2)].

17 PATIENT COUNSELING INFORMATION

Hypersensitivity Reactions Including Anaphylaxis and Infusion-Associated Reactions

Advise patients and caregivers that life-threatening hypersensitivity reactions, including anaphylaxis, and IARs may occur with CEREZYME treatment.

Advise patients and caregivers that anaphylaxis has occurred during the early course of enzyme replacement therapy and after extended duration of therapy.

Inform patients and caregivers of the symptoms of life-threatening hypersensitivity reactions, including anaphylaxis, and IARs and to seek immediate medical care should symptoms occur [see Warnings and Precautions (5.1, 5.2)].

Patient Registry

Inform patients and caregivers that the Gaucher patient registry has been established in order to better understand the variability and progression of Gaucher disease and to continue to monitor and evaluate long-term treatment effects of CEREZYME. A pregnancy sub-registry will also monitor the effects of CEREZYME on pregnant women and their offspring [see Use in Specific Populations (8.1)]. Encourage patients and caregivers to participate in the Gaucher patient registry. Advise patients that their participation is voluntary and may involve long-term follow-up. For information regarding the registry program, visit www.registrynxt.com or call 1-800-745-4447, extension 15500.

Manufactured by:
Genzyme Corporation
Cambridge, MA 02141
A SANOFI COMPANY
U.S. License Number: 1596

CEREZYME is a registered trademark of Genzyme Corporation.

PRINCIPAL DISPLAY PANEL - 400 Unit Vial Carton

NDC 58468-4663-1
Rx only

Cerezyme®
(imiglucerase) for injection

400 units per vial

For intravenous infusion after
reconstitution and dilution

sanofi